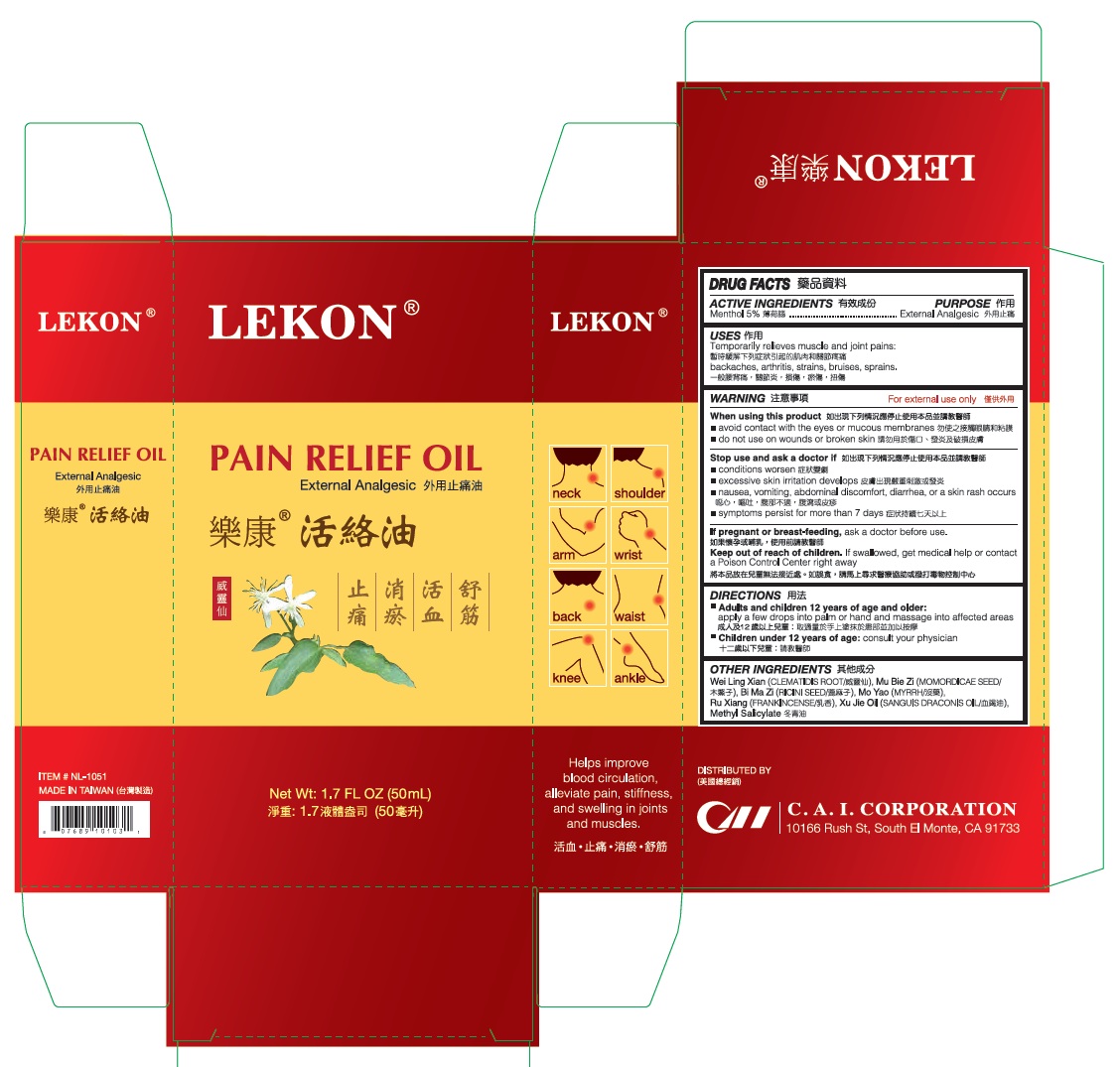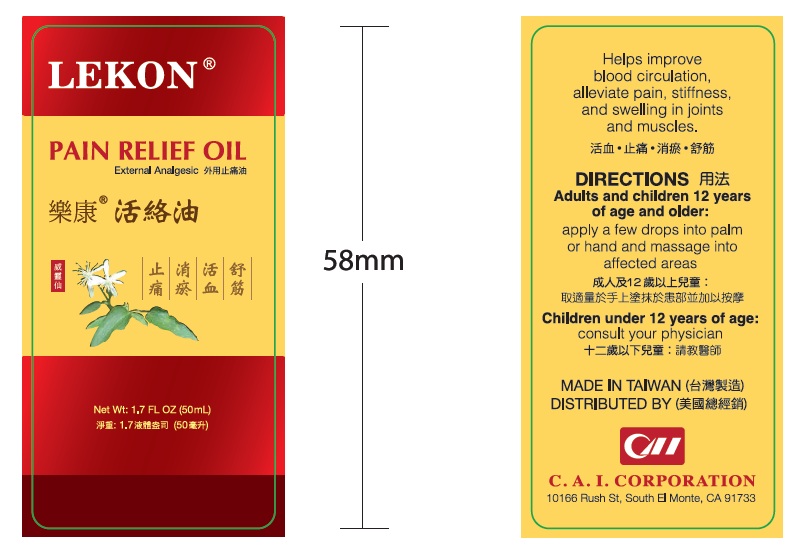 DRUG LABEL: Lekon Pain Relief Oil
NDC: 85954-001 | Form: OIL
Manufacturer: CAI Industries Corp.
Category: otc | Type: HUMAN OTC DRUG LABEL
Date: 20250821

ACTIVE INGREDIENTS: LEVOMENTHOL 5 g/100 mL
INACTIVE INGREDIENTS: CLEMATIS TERNIFLORA VAR. MANDSHURICA ROOT; MOMORDICA COCHINCHINENSIS SEED; RICINUS COMMUNIS SEED; MYRRH; FRANKINCENSE; METHYL SALICYLATE

Active Ingredients

Menthol 5%

Purpose

External analgesic

Uses

Temporarily relieves muscle and joint pains: backaches, arthritis, strains, bruises, sprains

Warnings

For external use only

When using this product

- avoid contact with the eyes or mucous membranes
- do not use on wounds or broken skin

Stop use and ask a doctor if

- conditions worsen
- excessive skin irritation develops
- nausea, vomiting, abdominal discomfort, diarrhea, or a skin rash occurs
- symptoms persists for more than 7 days

If pregnant or breast-feeding, ask a doctor before use.

Keep out of reach of children. If swallowed, get medical help or contact a Poison Control Center right away.

Directions

- Adults and children 12 years of age and older: apply few drops into palm or hand nad massage into affected areas
- Children under 12 years of age: consult your physician

Inactive ingredients

CLEMATIS TERNIFLORA VAR. MANDSHURICA ROOT, MOMORDICA COCHINCHINENSIS SEED, RICINUS COMMUNIS SEED, MYRRH, FRANKINCENSE, METHYL SALICYLATE